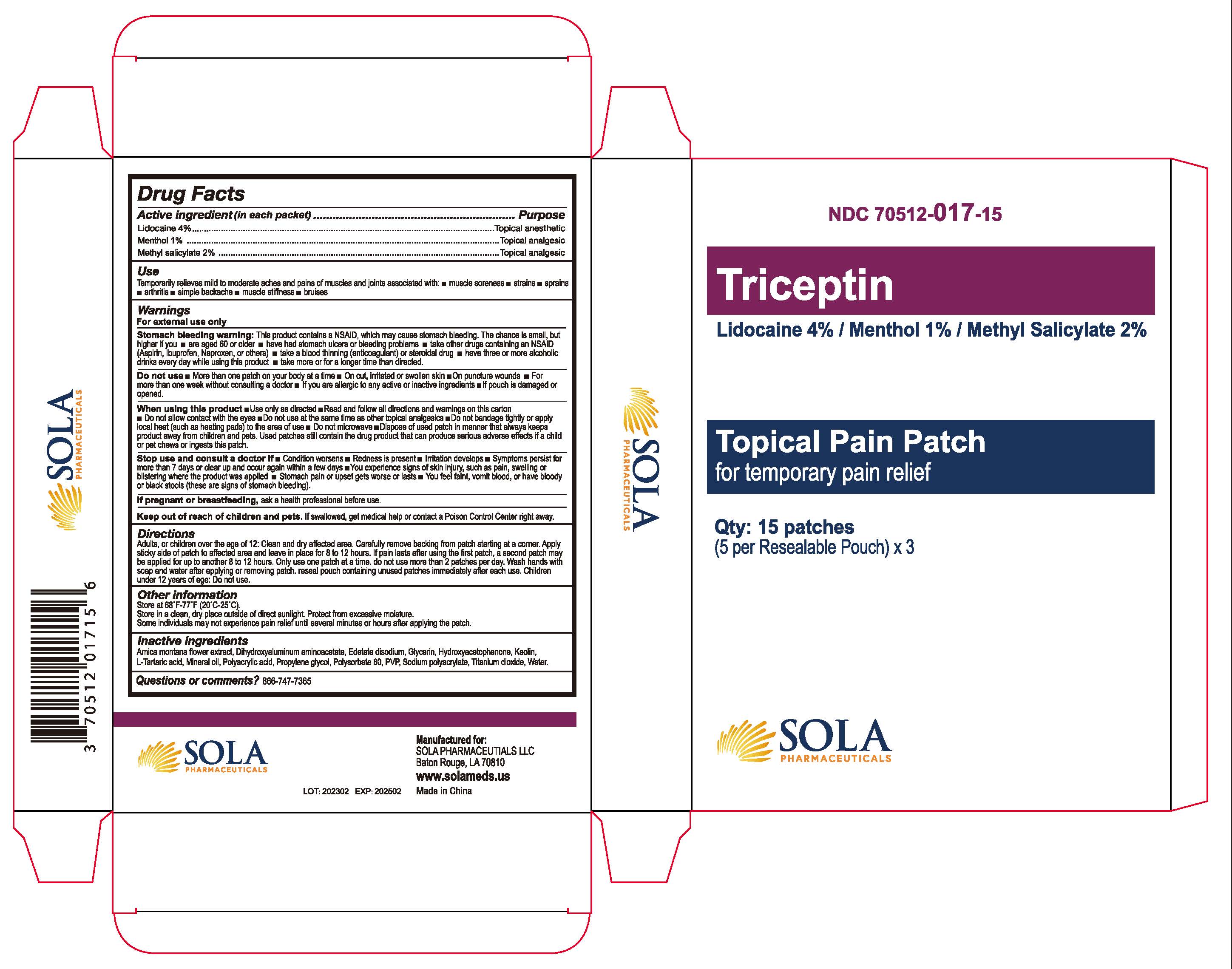 DRUG LABEL: Triceptin
NDC: 70512-017 | Form: PATCH
Manufacturer: SOLA Pharmaceuticals
Category: otc | Type: HUMAN OTC DRUG LABEL
Date: 20251208

ACTIVE INGREDIENTS: LIDOCAINE 40 mg/1 g; METHYL SALICYLATE 20 mg/1 g; MENTHOL 10 mg/1 g
INACTIVE INGREDIENTS: ARNICA MONTANA FLOWER; PROPYLENE GLYCOL; TITANIUM DIOXIDE; WATER; DIHYDROXYALUMINUM AMINOACETATE; EDETATE DISODIUM; GLYCERIN; MINERAL OIL; POLYACRYLIC ACID (250000 MW); POVIDONE K90; SODIUM POLYACRYLATE (2500000 MW); HYDROXYACETOPHENONE; KAOLIN; TARTARIC ACID; POLYSORBATE 80

Triceptin Patch

Active ingredient (in each packet)

Lidocaine 4%

Purpose

Topical anesthetic

Active ingredient (in each packet)

Menthol 1%

Purpose

Topcial analgesic

Active ingredient (in each packet)

Methyl salicylate 2%

Purpose

Topcial analgesic

Use

Temporarily relieves mild to moderate aches and pains of muscles and joints associated with:

- Muscle soreness
- strains
- sprains
- arthritis
- simple backache
- muscle stiffness
- bruises

Warnings

For external use only

Stomach bleeding warning: This product contains a NSAID, which may cause stomach bleeding. The chance is small, but higher if you

- are aged 60 or older
- have had stomach ulcers or bleeding problems
- take other drugs containing an NSAID (Aspirin, ibuprofen, Naproxen, or others)
- take a blood thinning (anticoagulant) or steroidal drug
- have three or more alcholic drinks every day while using this product
- take more or for a longer time than directed

Do not use

- More than one patch on your body at a time
- On cut, irritated or swollen skin
- On puncture wounds
- For more than one week without consulting a doctor
- If you are allergic to any active or inactive ingredients
- If pouch is damaged or opened

When using this product

- Use only as directed
- Read and follow all directions and warnings on this carton
- Do not allow contact with the eyes
- Do not use at the same time as other topical analgesics
- Do not bandage tightly or apply local heat (such as heating pads) to the area of use
- Do no microwave
- Dispose of used patch in manner that always keeps product away from children and pets. Used patches still contain the drug product that can produce serious adverse effects if a child or pet chews or ingests this patch.

Stop use and consult a doctor if

- Condition worsens
- Redness is present
- Irritation develops
- Symptoms persist for more than 7 days or clear up and occur again within a few days
- You experience signs of skin injury, such as pain, swelling, or blistering where the product was applied
- Stomach pain or upset gets worst or lasts
- You feel faint, vomit blood, or have bloody or black stools (these are signs or stomach bleeding).

If pregnant or breastfeeding

ask a healthcare professional before use.

Keep out of reach of children and pets.

If swallowed, get medical help or contact a Poison Control Center right away.

Directions

Adults, or children over the age of 12: Clean and dry affected area. Carefully remove backing from patch starting at a corner. Apply sticky side of patch to affected area and leave in place for 8 to 12 hours. If pain lasts after using the first patch, a second patch may be applied for up to another 8 to 12 hours. Only use one patch at a time. do not use more than 2 patches per day. Wash hands with soap and water after applying or removing patch. reseal pouch containing unnsed patches immediately after each use. Children under 12 years of age: Do not use.

Other information

Store at 68°F-77°F (20°C-25°C).

Store in a clean, dry place outside of direct sunlight. Protect from excessive mositure.

Some individuals may not experience pain relief until several minutes or hours after applying the patch.

Inactive ingredients

Arnica montana flower extract, Dihydroxyaluminum aminoacetate, Edetate disodium, Glycerin, Hydroxyacetophenone, Kaolin, L-Tartaric acid, Mineral oil, Polyacrylic acid, Propylene glycol, Polysorbate 80, PVP, Sodium polyacrylate, Titanium dioxide, Water.

Questions or comments?

866-747-7365

PACKAGE LABEL

Manufactured for:

SOLA PHARMACEUTICALS LLC

Baton Rouge, LA 70810

www.solameds.us

Made in China

Triceptin

Topical Pain Patch

for temporary pain relief

NDC 70512-017-15

Qty: 15 patches

(5 per Resealable Pouch) x 3